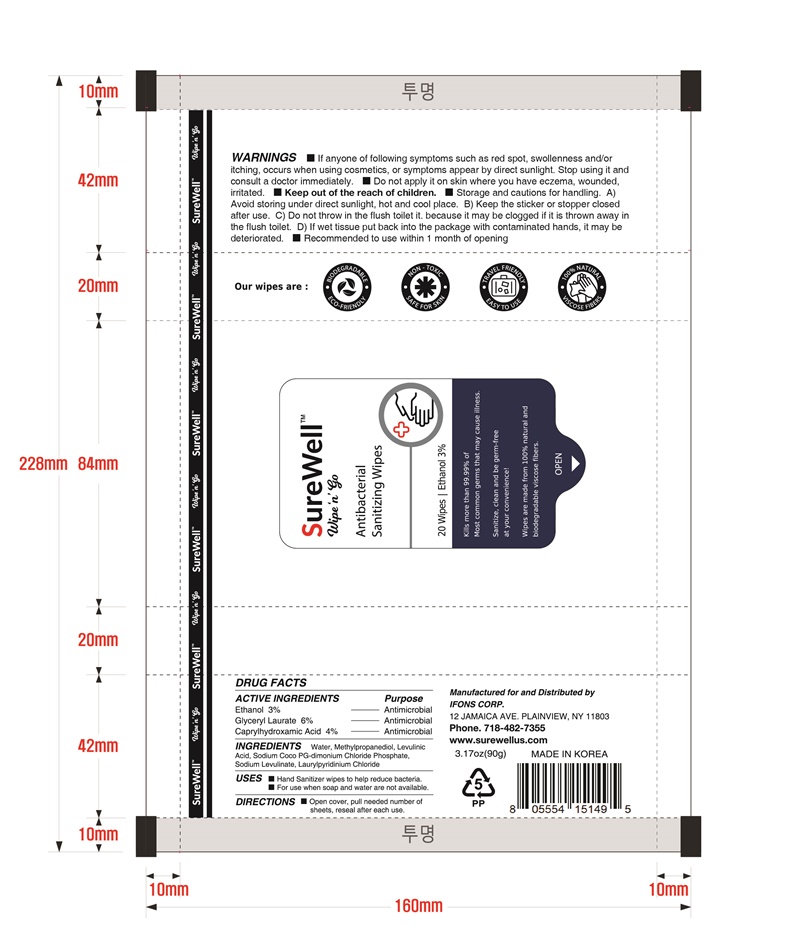 DRUG LABEL: SureWell Sanitizing Wipes
NDC: 79892-301 | Form: LIQUID
Manufacturer: Ifons Corp.
Category: otc | Type: HUMAN OTC DRUG LABEL
Date: 20200822

ACTIVE INGREDIENTS: ALCOHOL 3 g/100 g; GLYCERYL LAURATE 6 g/100 g; CAPRYLHYDROXAMIC ACID 4 g/100 g
INACTIVE INGREDIENTS: LAURYLPYRIDINIUM CHLORIDE 5 g/100 g; SODIUM LEVULINATE 5 g/100 g; COCOTRIMONIUM CHLORIDE; LEVULINIC ACID; WATER; METHYLPROPANEDIOL

ACTIVE INGREDIENT

ALCOHOL, GLYCERYL LAURATE, SODIUM LEVULINATE, LAURYLPYRIDINIUM CHLORIDE, CAPRYLHYDROXAMIC ACID

PURPOSE

ANTIMICROBIAL

direction

Open cover, pull needed number of sheets, reseal after each use.

Do not use: Do not apply it on skin where you have eczema, wounded, irritated.

storage and cautions for handling
A) Avoid storing under direct sunlight, hot and cool place.
B) keep the sticker or stopper closed after use.
C) Do not throw in the flush toilet it. because it may be clogged if it is thrown away in the flush toilet
D) If wet tissue put back into the package with contaminated hands, it may be deteriorated.
recommended to use within 1 month of opening.

Stop use and ask a doctor,

If anyone of following symptoms such as red spot, swollenness and/or itching, occurs when using cosmetics, or symptoms appear by direct sunlight. stop using it and consult a doctor immediately.

Keep out of reach of children

INDICATION

Place enough product on hands to cover all surfaces. Rub hands together until dry.

Supervise children under 6 years of age when using this product to avoid swallowing.

Inactive

Water, Methylpropanediol, Sodium coco pg-dimonium chloride phosphate, Levulinic acid

label

79892-301-01